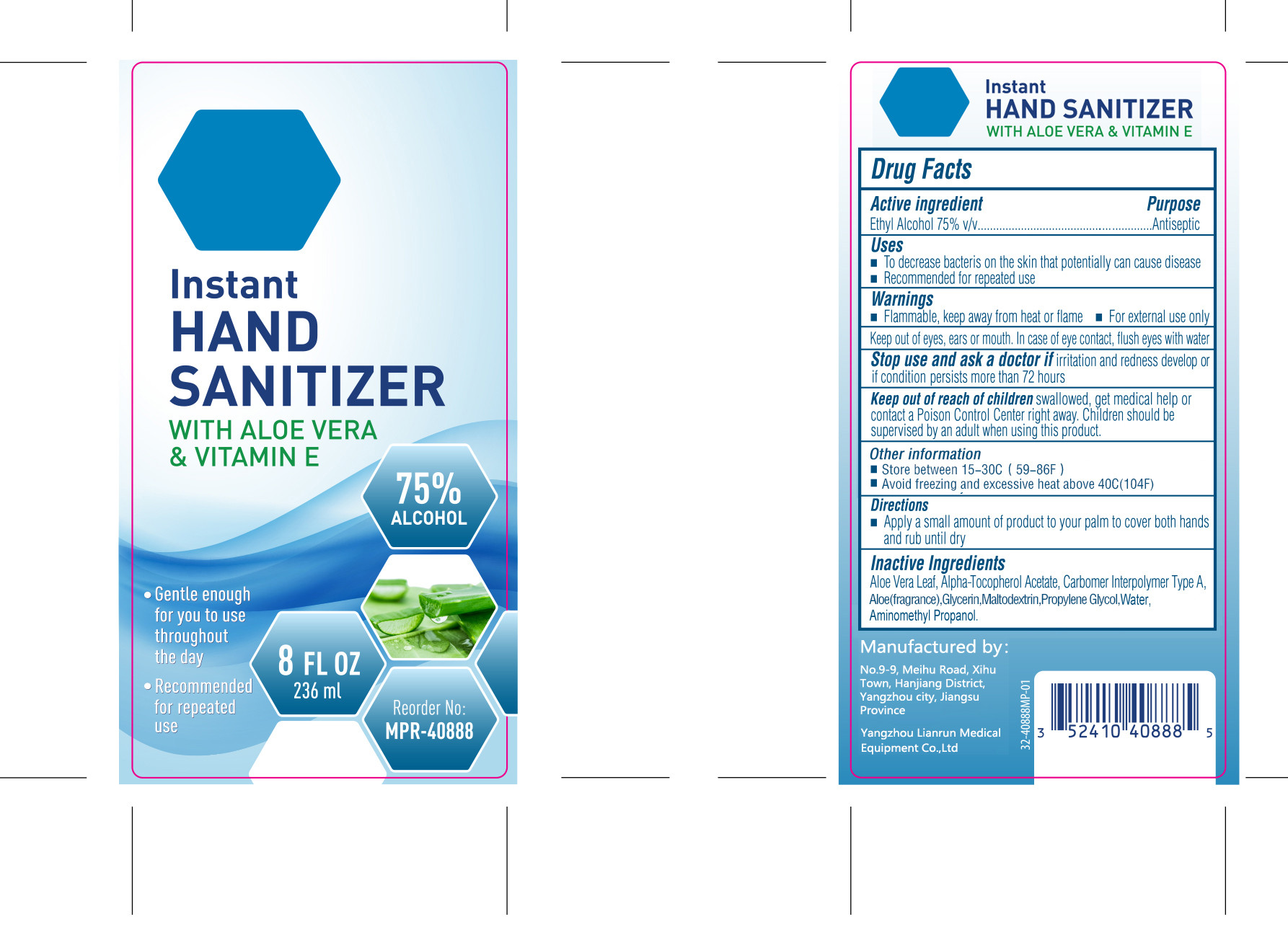 DRUG LABEL: Hand sanitizer
NDC: 93782-001 | Form: GEL
Manufacturer: Yangzhou Lianrun Medical Equipment Co., Ltd.
Category: otc | Type: HUMAN OTC DRUG LABEL
Date: 20201117

ACTIVE INGREDIENTS: ALCOHOL 75 mL/100 mL
INACTIVE INGREDIENTS: ALOE; GLYCERIN; MALTODEXTRIN; WATER; ALOE VERA LEAF; .ALPHA.-TOCOPHEROL ACETATE; AMINOMETHYLPROPANOL; CARBOMER COPOLYMER TYPE A; PROPYLENE GLYCOL

ACTIVE INGREDIENT

Ethyl Alcohol 75%

PURPOSE

Antiseptic

Uses

To decrease bacteris on the skin that potentially can cause disease

Recommended for repeated use

WARNINGS

Flammable, keep away from heat or flame

For external use only

Keep out of eyes, ears or mouth. In case of eye contact, flush eyes with water

Stop use and ask a doctor if irritation and redness develop or if condition persists more than 72 hours

Keep out of reach of children swallowed, get medical help or contact a Poison Control Center right away. Children should be supervised by an adult when using this product.

Other information

Store between 15-30°C(59-86°F)
Avoid freezing and excessive heat above 40°C(104°F)

Directions

Apply a small amount of product to your palm to cover both hands and rub until dry.

INACTIVE INGREDIENT

Aloe VeraLeaf, Alpha-Tocopherol Acetate, Carbomer Interpolymer Type A,Aloe(fragrance),Glycerin.Maltodextrin,Propylene Glycol,Water,Aminomethyl Propanol.